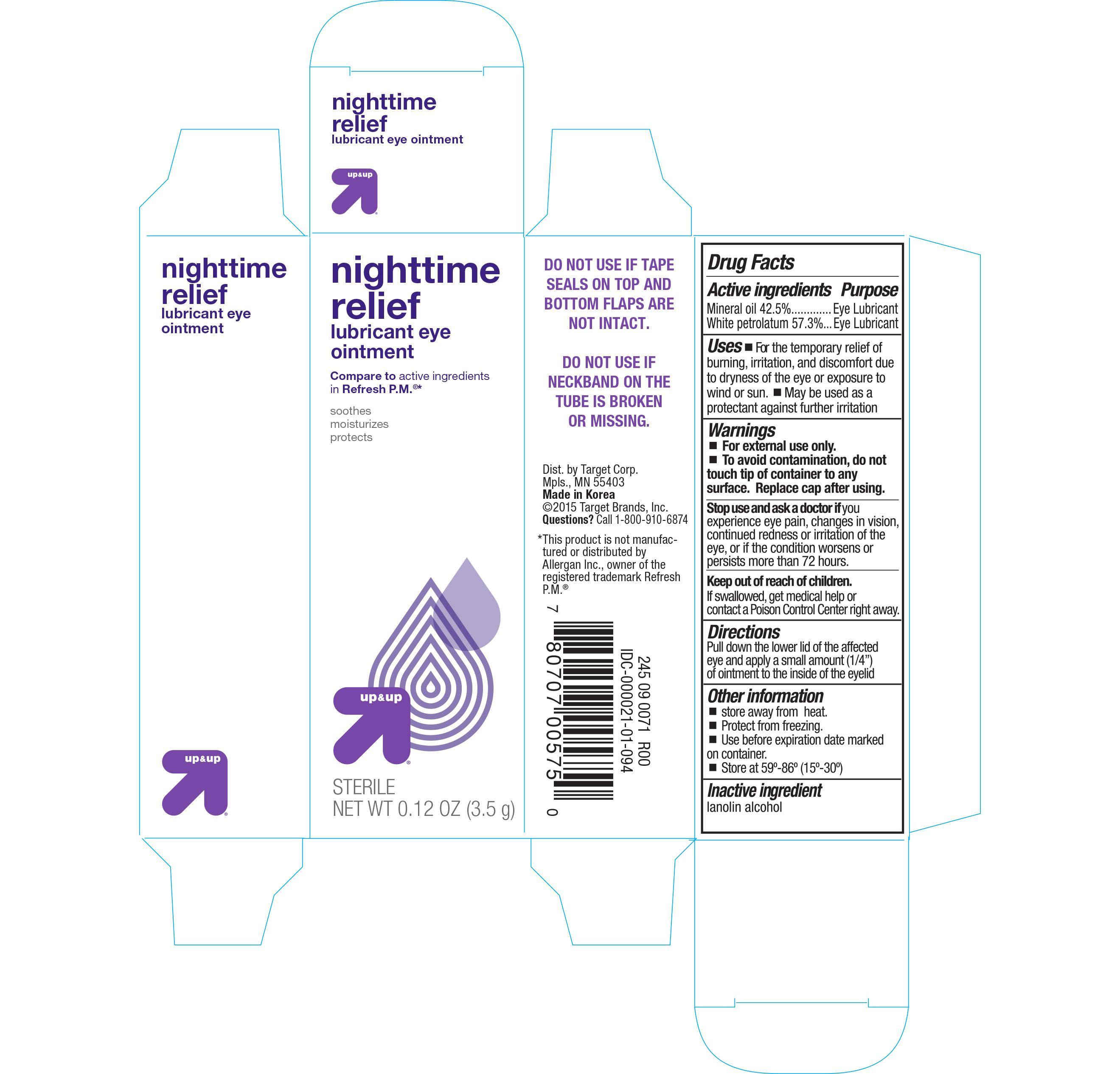 DRUG LABEL: Nightime Relief Lubricant Eye
NDC: 11673-575 | Form: OINTMENT
Manufacturer: Target Corporation
Category: otc | Type: HUMAN OTC DRUG LABEL
Date: 20150305

ACTIVE INGREDIENTS: MINERAL OIL 425 mg/1 g; PETROLATUM 533 mg/1 g
INACTIVE INGREDIENTS: LANOLIN ALCOHOLS

Active ingredients Purpose

Mineral oil 42.5%........................................................ Eye Lubricant

White petrolatum 57.3%.............................................. Eye Lubricant

Uses

- For the temporary relief of burning, irritation, and discomfort due to dryness or the eye or exposure to wind or sun.
- May be used as a protectant against further irritation

Warnings

- For external use only.
- To avoid contamination, do not touch tip of contaainer to any surface. Replace cap after using.

Stop use and ask a doctor if you experience eye pain, changes in vision, continued reness or irritation of the eye, or if the condition worsens or persists more than 72 hours.

Keep out of reach of children.

If swallowed, get medical help or contact a Poison Control Center right away.

Directions

Pull down the lower lid of the affected eye and apply a small amount (1/4") of ointment to the inside of the eyelid

Other information

- store away from heat
- protect from freezing
- use before expiration date marked on container
- store at 59°-86° (15°-30°)

Inactive ingredient

lanolin alcohol

DOSAGE AND ADMINISTRATION

DISTRIBUTED BY:

TARGET CORP.

MINNEAPOLIS, MN 55403

MADE IN KOREA